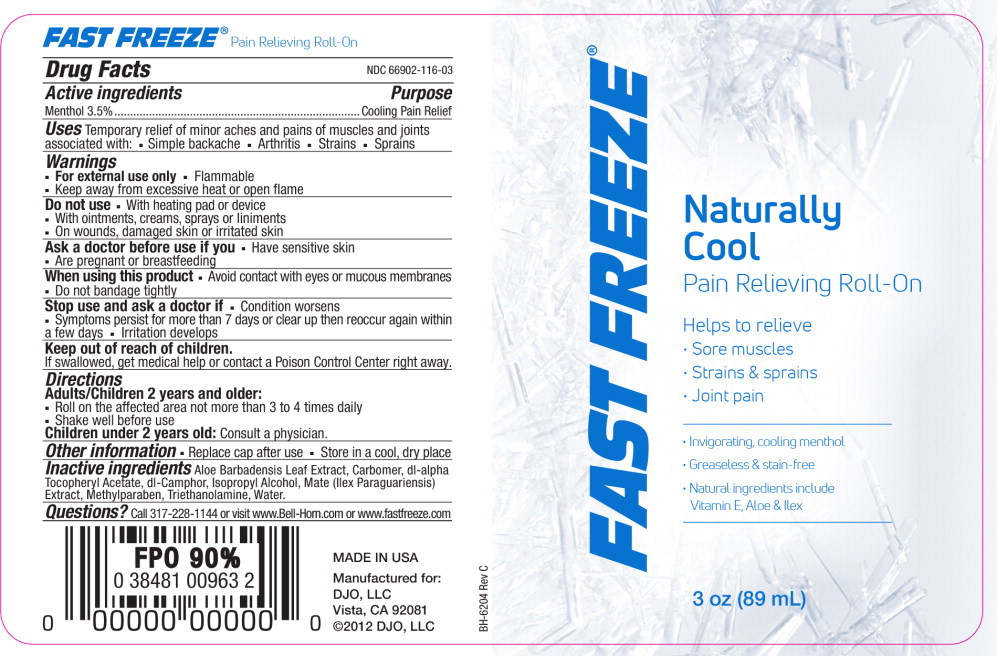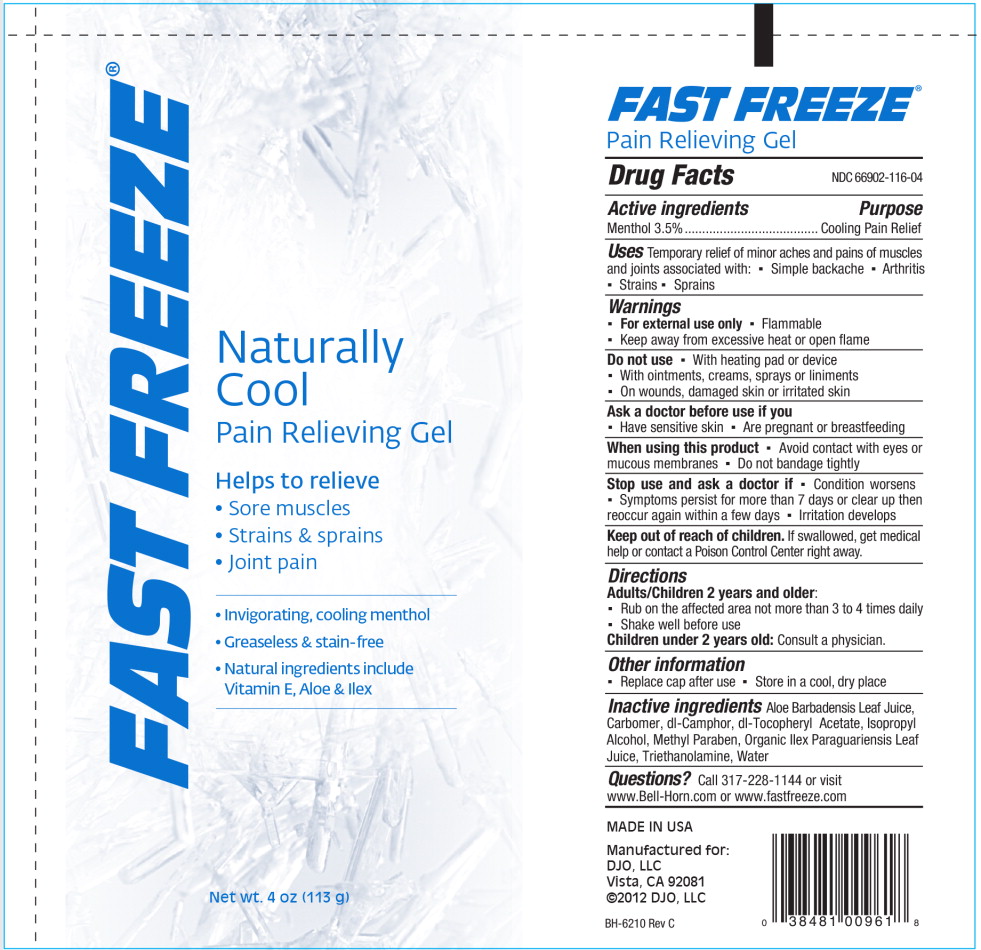 DRUG LABEL: Fast Freeze Pain Relieving
NDC: 66902-116 | Form: GEL
Manufacturer: NATURAL ESSENTIALS, INC.
Category: otc | Type: HUMAN OTC DRUG LABEL
Date: 20250818

ACTIVE INGREDIENTS: MENTHOL, UNSPECIFIED FORM 33 mg/1 mL
INACTIVE INGREDIENTS: ALOE VERA LEAF; CARBOMER HOMOPOLYMER TYPE C (ALLYL PENTAERYTHRITOL CROSSLINKED); CAMPHOR (SYNTHETIC); .ALPHA.-TOCOPHEROL ACETATE; ISOPROPYL ALCOHOL; METHYLPARABEN; ILEX PARAGUARIENSIS LEAF; TROLAMINE; WATER

Fast Freeze NDC 66902-116 Drug Facts

Active ingredients

Menthol 3.5%

Purpose

Cooling Pain Relief

Uses

Temporary relief of minor aches and pains of muscles and joints associated with:

- Simple backache
- Arthritis
- Strains
- Sprains

Warnings

- For external use only
- Flammable
- Keep away from excessive heat or open flame

Do not use

- With heating pad or device
- With ointments, creams, sprays or liniments
- On wounds, damaged skin or irritated skin

Ask a doctor before use if you

- Have sensitive skin
- Are pregnant or breastfeeding

When using this product

- Avoid contact with eyes or mucous membranes
- Do not bandage tightly

Stop use and ask a doctor if

- Condition worsens
- Symptoms persist for more than 7 days or clear up then reoccur again within a few days
- Irritation develops

Keep out of reach of children.

If swallowed, get medical help or contact a Poison Control Center right away.

Directions

Adults/Children 2 years and older:

- Roll on the affected area not more than 3 to 4 times daily
- Shake well before use

Children under 2 years old:Consult a physician.

Other information

- Replace cap after use
- Store in a cool, dry place

Inactive ingredients

Aloe Barbadensis Leaf Extract, Carbomer, dl-alpha Tocopheryl Acetate, dl-Camphor, Isopropyl Alcohol, Mate (Ilex Paraguariensis) Extract, Methylparaben, Triethanolamine, Water.

Questions?

Call 317-228-1144 or visit www.Bell-Horn.com or www.fastfreeze.com

Principal Display Panel - 89 mL Container Label

FAST FREEZE®

Naturally
Cool
Pain Relieving Roll-On

Helps to relieve

- Sore muscles
- Strains & sprains
- Joint pain
- Invigorating, cooling menthol
- Greaseless & stain-free
- Natural ingredients include
  Vitamin E, Aloe & Ilex

3 oz (89 mL)

Principal Display Panel - 120 mL Tube Label

FAST FREEZE®

Naturally
Cool
Pain Relieving Gel

Helps to relieve

- Sore muscles
- Strains & sprains
- Joint pain
- Invigorating, cooling menthol
- Greaseless & stain-free
- Natural ingredients include
  Vitamin E, Aloe & Ilex

Net wt. 4 oz (113 g)